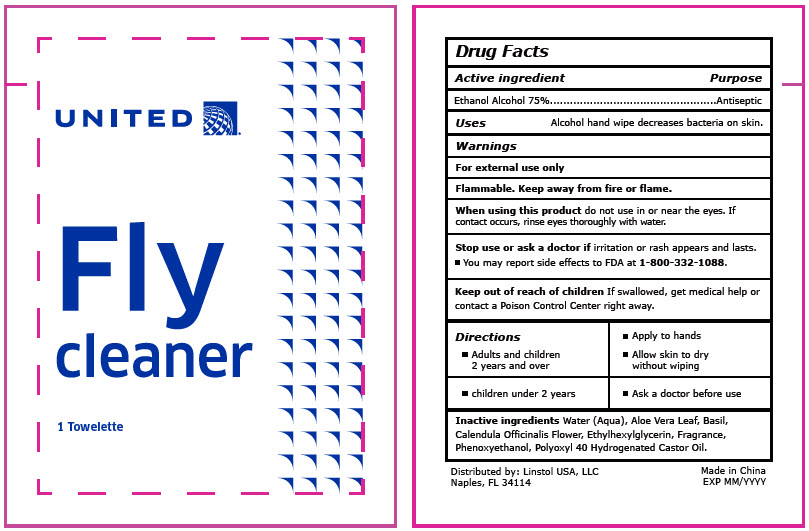 DRUG LABEL: United Airlines Fly Cleaner
NDC: 76982-3866 | Form: CLOTH
Manufacturer: Linstol USA, LLC
Category: otc | Type: HUMAN OTC DRUG LABEL
Date: 20221221

ACTIVE INGREDIENTS: ALCOHOL 75 mL/100 mL
INACTIVE INGREDIENTS: WATER; ALOE VERA LEAF; BASIL; CALENDULA OFFICINALIS FLOWER; ETHYLHEXYLGLYCERIN; FRAGRANCE LAVENDER & CHIA F-153480; PHENOXYETHANOL; POLYOXYL 40 HYDROGENATED CASTOR OIL

United Airlines Fly Cleaner

Drug Facts

Active ingredient

Ethanol Alcohol 75%

Purpose

Antiseptic

Uses

Alcohol hand wipe decreases bacteria on skin.

Warnings

For external use only

Flammable. Keep away from fire or flame.

When using this product do not use in or near the eyes. If contact occurs, rinse eyes thoroughly with water.

Stop use or ask a doctor if irritation or rash appears and lasts.

- You may report side effects to FDA at 1-800-332-1088.

Keep out of reach of children If swallowed, get medical help or contact a Poison Control Center right away.

DOSAGE AND ADMINISTRATION

Directions; - Adults and children 2 years and over | - Apply to hands - Allow skin to dry without wiping
- children under 2 years | - Ask a doctor before use

Inactive ingredients

Water (Aqua), Aloe Vera Leaf, Basil, Calendula Officinalis Flower, Ethylhexylglycerin, Fragrance, Phenoxyethanol, Polyoxyl 40 Hydrogenated Castor Oil.

Distributed by: Linstol USA, LLC
Naples, FL 34114

PRINCIPAL DISPLAY PANEL - 1 Towelette Packet Label

UNITED®

Fly
cleaner

1 Towelette